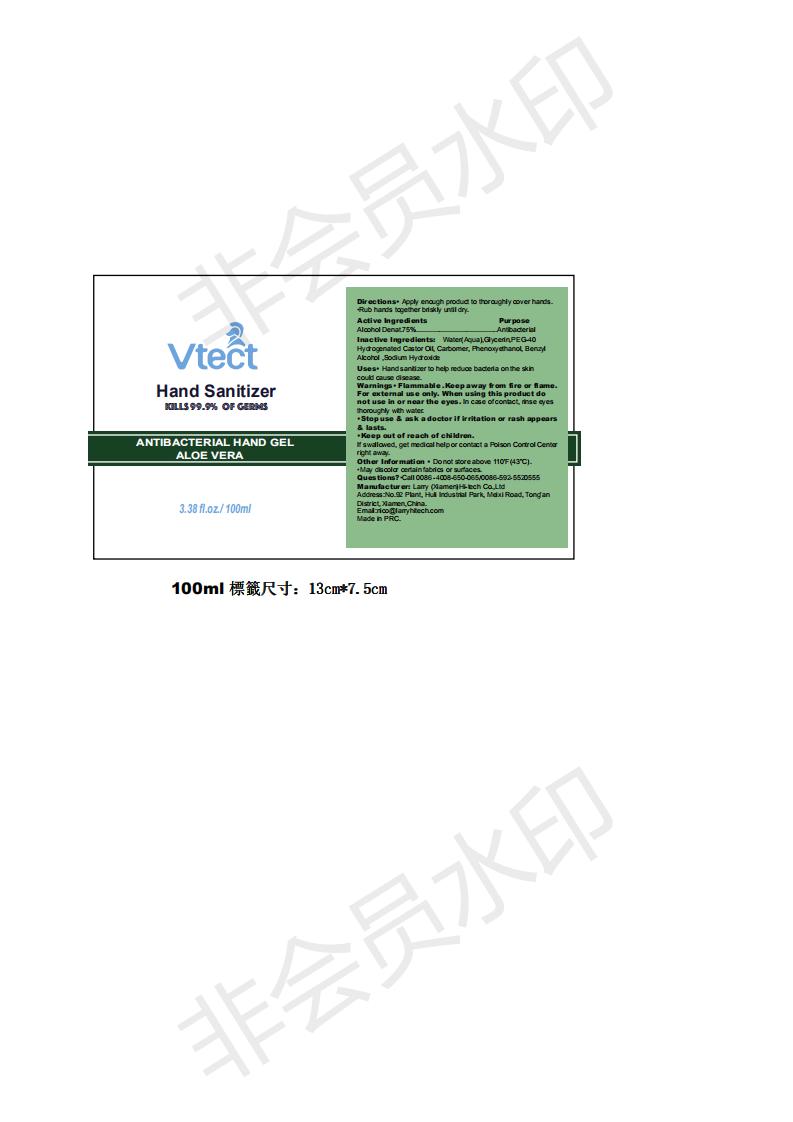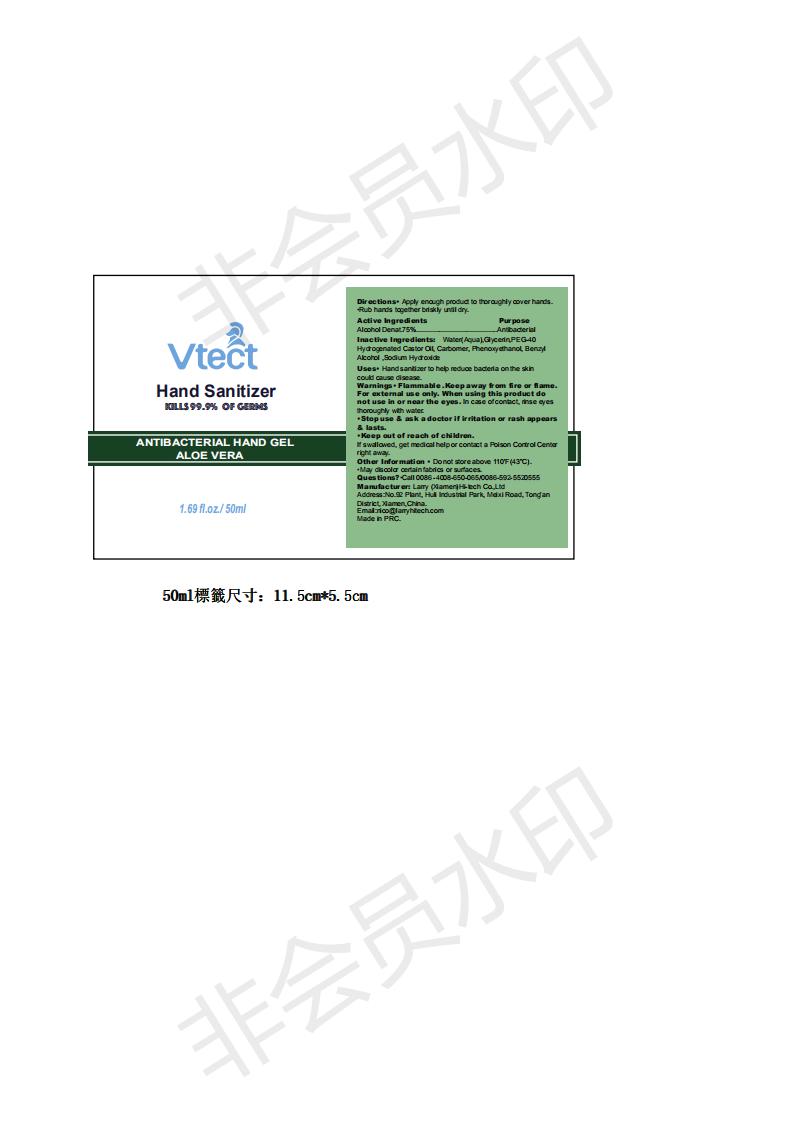 DRUG LABEL: Hand Sanitizer
NDC: 73166-005 | Form: GEL
Manufacturer: Larry (Xiamen)Hi-Tech Co.,Ltd.
Category: otc | Type: HUMAN OTC DRUG LABEL
Date: 20200423

ACTIVE INGREDIENTS: ALCOHOL 75 mL/100 mL
INACTIVE INGREDIENTS: SODIUM HYDROXIDE; CARBOMER 934; GLYCERIN; POLYOXYL 40 HYDROGENATED CASTOR OIL; BENZYL ALCOHOL; PHENOXYETHANOL

Hand Sanitizer

Directions

Apply enough product to thoroughly cover hands.Rub hands together briskly until dry

Active Ingredients

Alcohol Denat.75%

Inactive Ingredients

Water(Aqua),Glycerin,PEG-40 Hydrogenated Castor Oil, Carbomer, Phenoxyethanol, Benzyl Alcohol ,Sodium Hydroxide

Uses

Hand sanitizer to help reduce bacteria on the skin could cause disease.

Warnings

Flammable .Keep away from fire or flame.For external use only. When using this product do not use in or near the eyes. In case of contact, rinse eyesthoroughly with water.

Stop use and ask a doctor if irritation or rash appears and lasts.

Keep out of reach of children.

If swallowed, get medical help or contact a Poison Control Center right away.

Other Information

Do not store above 110F(43C).

May discolor certain fabrics or surfaces.

Purpose

Purpose Antibacterial